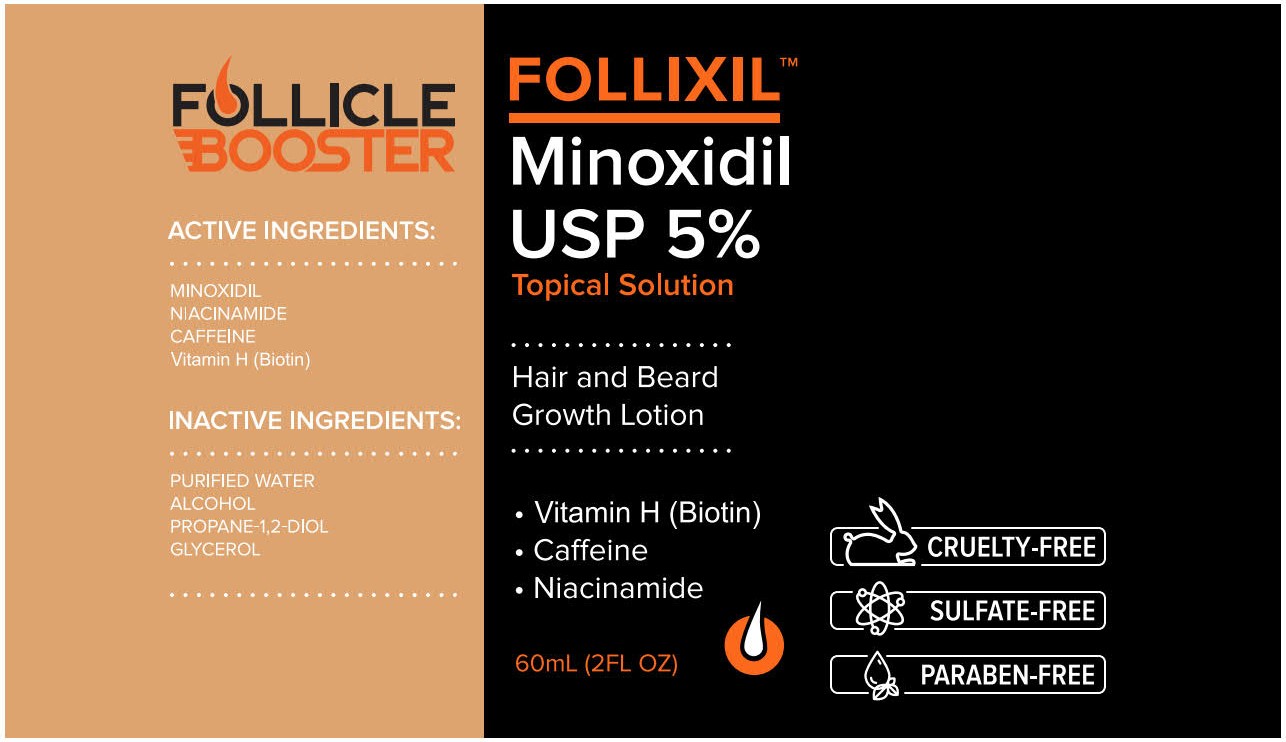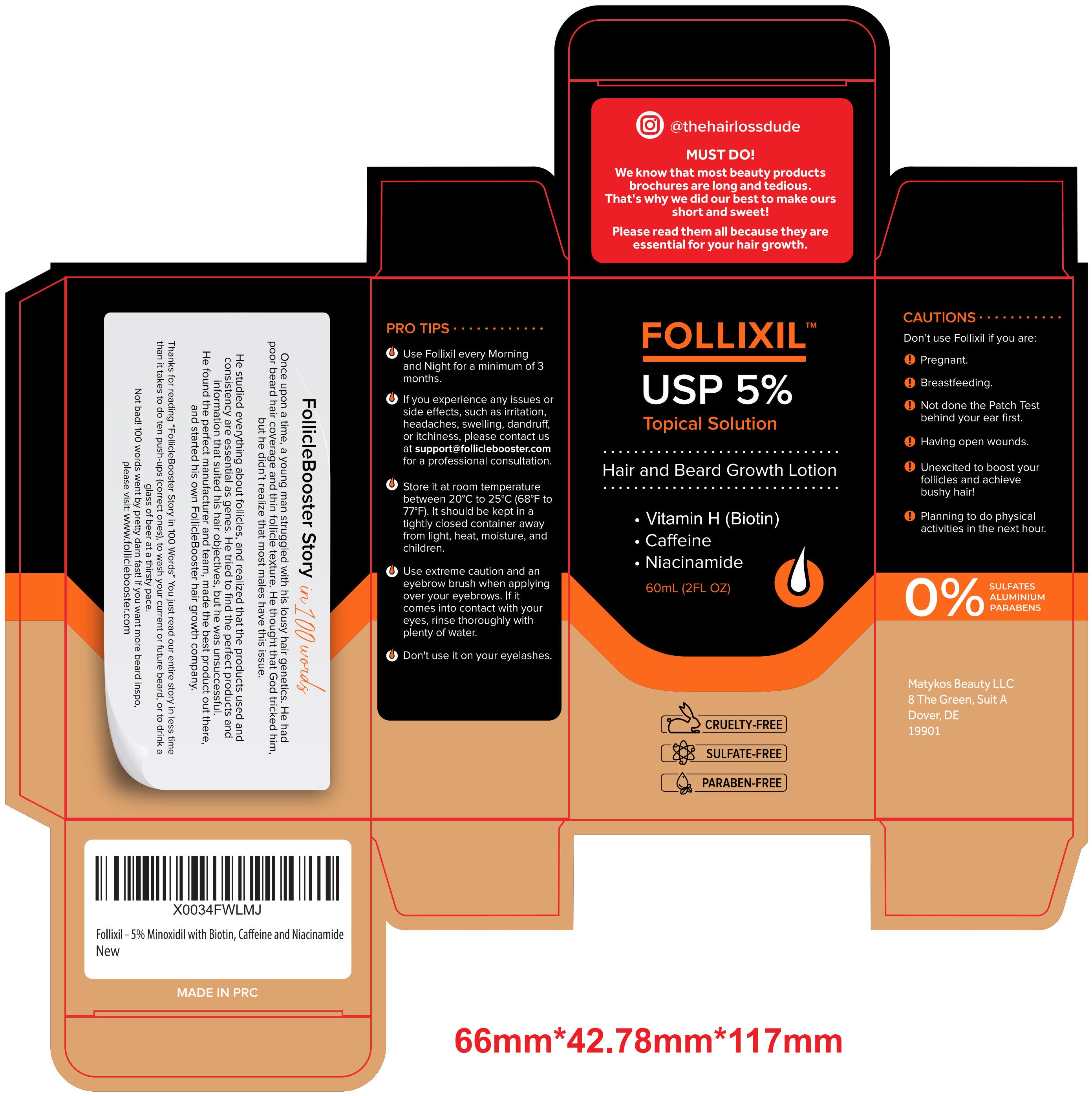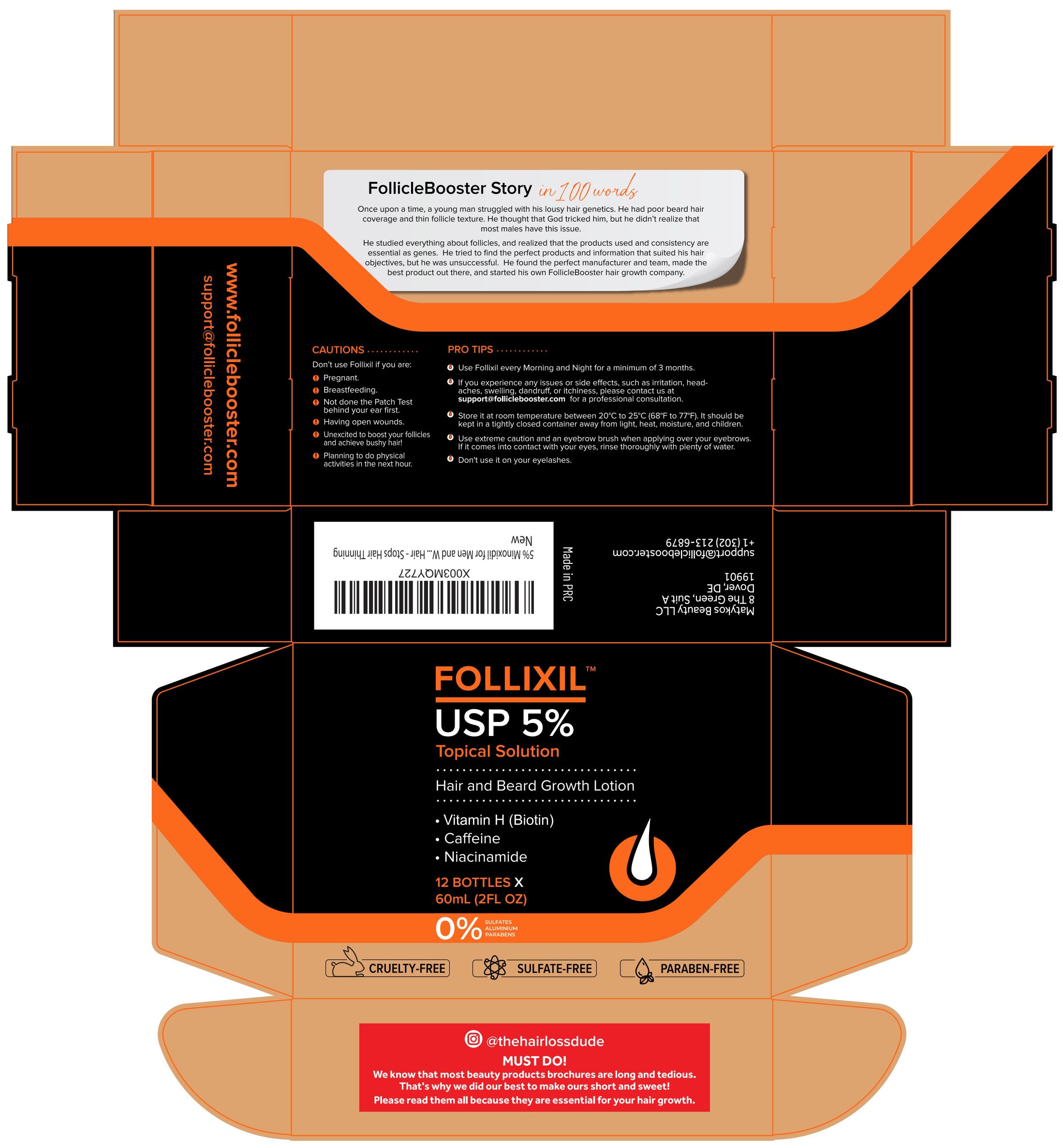 DRUG LABEL: FOLLIXIL Hair and Beard Growth-Lotion
NDC: 83835-211 | Form: LIQUID
Manufacturer: Matykos Beauty LLC
Category: otc | Type: HUMAN OTC DRUG LABEL
Date: 20231228

ACTIVE INGREDIENTS: MINOXIDIL 5 g/100 mL
INACTIVE INGREDIENTS: ALCOHOL; CAFFEINE; PROPYLENE GLYCOL; BIOTIN; GLYCERIN; NIACINAMIDE; WATER

FB-006

ACTIVE INGREDIENT

Minoxidil 5%

PURPOSE

Help hair and beard growth

Don't use Follixil if you are:

- Pregnant.
- Breastfeeding.
- Not done the Patch Test behind your ear first.
- Having open wounds.
- Unexcited to boost your follicles and achieve bushy hair!
- Planning to do physical activities in the next hour.

STOP USE

If you experience any issues or side effects, such as irritation, headaches, swelling, dandruff, or itchiness, please contact us at support@folliclebooster.com for a professional consultation.

WHEN USING

Use extreme caution and an eyebrow brush when applying over your eyebrows. If it comes into contact with your eyes, rinse thoroughly with plenty of water.

Don't use it on your eyelashes.

KEEP OUT OF REACH OF CHILDREN

It should be kept in a tightly closed container away from light, heat, moisture, and children.

WARNINGS

Use extreme caution and an eyebrow brush when applying over your eyebrows. If it comes into contact with your eyes, rinse thoroughly with plenty of water.

Don't use it on your eyelashes.

DOSAGE AND ADMINISTRATION

Apply 1 mL twice a day. Once in the morning and another time in the evening before bed. Use only on fully dry hair. Apply directly on top of the scalp of hair loss area.

Use Follixil every Morning and Night for a minimum of 3 months.

INDICATIONS AND USAGE

Prevent and Stop Hair Loss; Stimulate Hair Growth; Improve Fullness of Hair; Restore Vitality of Hair; Strengthen and Activate Hair Follicles.

STORAGE AND HANDLING

Store it at room temperature between 20℃ to 25℃ (68℉ to 77℉). It should be kept in a tightly closed container away from light, heat, moisture, and children.

INACTIVE INGREDIENT

Niacinamide, Caffeine, Vitamin H (Biotin), Purified Water, Alcohol, Propane-1,2-Diol, Glycerol